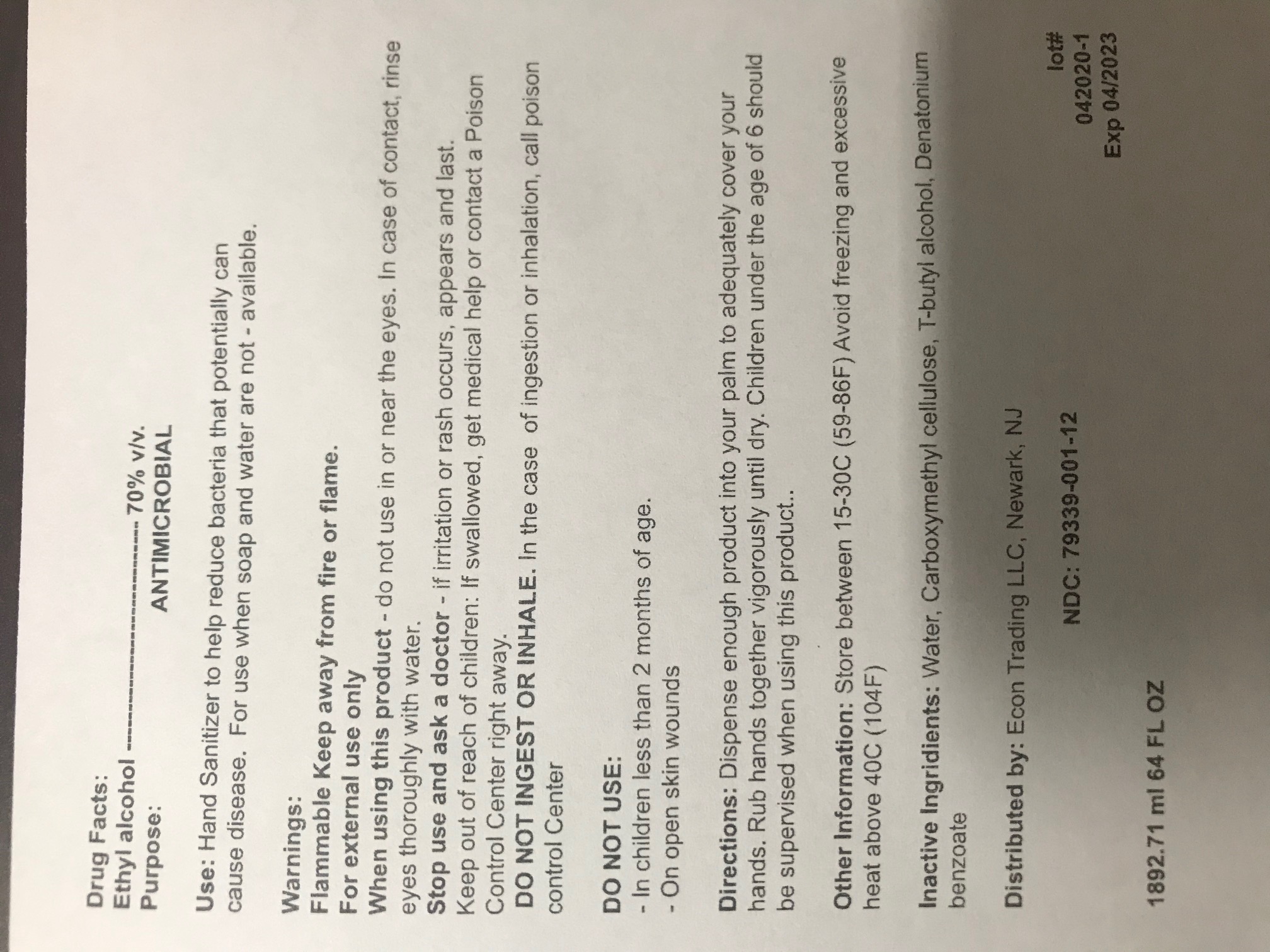 DRUG LABEL: ManiPure Hand Sanitizer
NDC: 79339-001 | Form: LIQUID
Manufacturer: ECON TRADING LLC
Category: otc | Type: HUMAN OTC DRUG LABEL
Date: 20200630

ACTIVE INGREDIENTS: ALCOHOL 70 mL/100 mL
INACTIVE INGREDIENTS: TERT-BUTYL ALCOHOL 0.0875 mL/100 mL; DENATONIUM BENZOATE 0.001 mL/100 mL; CARBOXYMETHYLCELLULOSE SODIUM 0.8 mL/100 mL; WATER 28.2 mL/100 mL

Drug Facts:

Ethyl alcohol ----------------------------- 70% v/v.

Porpuse

ANTIMICROBIAL

Use:

Hand Sanitizer to help reduce bacteria that potentially can

cause disease. For use when soap and water are not - available.

Warnings:

Flammable Keep away from fire or flame.

For external use only

When using this product - do not use in or near the eyes. In case of contact, rinse eyes thoroughly with water. DO NOT INGEST OR INHALE. In the case of ingestion or inhalation, call poison control Center

DO NOT USE:

- In children less than 2 months of age.

- On open skin wounds

Stop use and ask a doctor

- if irritation or rash occurs, appears and last.

Keep out of reach of children: If swallowed, get medical help or contact a Poison Control Center right away.

Directions:

Dispense enough product into your palm to adequately cover your hands. Rub hands together vigorously until dry. Children under the age of 6 should be supervised when using this product..

Other Information:

Store between 15-30C (59-86F) Avoid freezing and excessive heat above 40C (104F)

Inactive Ingridients:

Water, Carboxymethyl cellulose, T-butyl alcohol, Denatonium benzoate

Package.Label Principal Display Panel

Drug Facts
Ethyl alcohol ----------------- 70% v/v.
Purpose: ANTIMICROBIAL

Indications : Hand Sanitizer to help
reduce bacteria that potentially can
cause disease. For use when soap and
water are not - available.

Warnings: Flammable Keep away from
fire or flame.For external use only When
using this product do not use in or near
the eyes. In case of contact, rinse eyes
thoroughly with water. DO NOT INGEST
OR INHALE. In the case of ingestion or
inhalation, call poison control.
DO NOT USE:
- In children less than 2 months of age
- On open skin wounds

When using this product: keep out of
eyes, ears, and mouth. In case of contact
with eyes, rinse eyes thoroughly with
water. Stop use and ask a doctor if irritation
or rash occurs. These may be signs of a
serious condition.

Keep out of reach of children. If swallowed, get medical help or
contact a Poison Control Center right away

Directions: Dispense enough product into
your palm to adequately cover your hands
. Rub hands together vigorously until dry.
Children under the age of 6 should be
supervised when using this product.

.Other Information:
Store between 15-30C (59-86F)
Avoid freezing and excessive
heat above 40C (104F)

Inactive Ingridients:
Water, Carboxymethyl cellulose,
T-butyl alcohol, Denatonium benzoate

Distributed by:
Econ Trading LLC,
Newark, NJ
1892.71 ml 64 FL OZ
lot# 042020-1 Exp 04/2023

1892.71 ml 64 FL OZ NDC: 79339-001-12